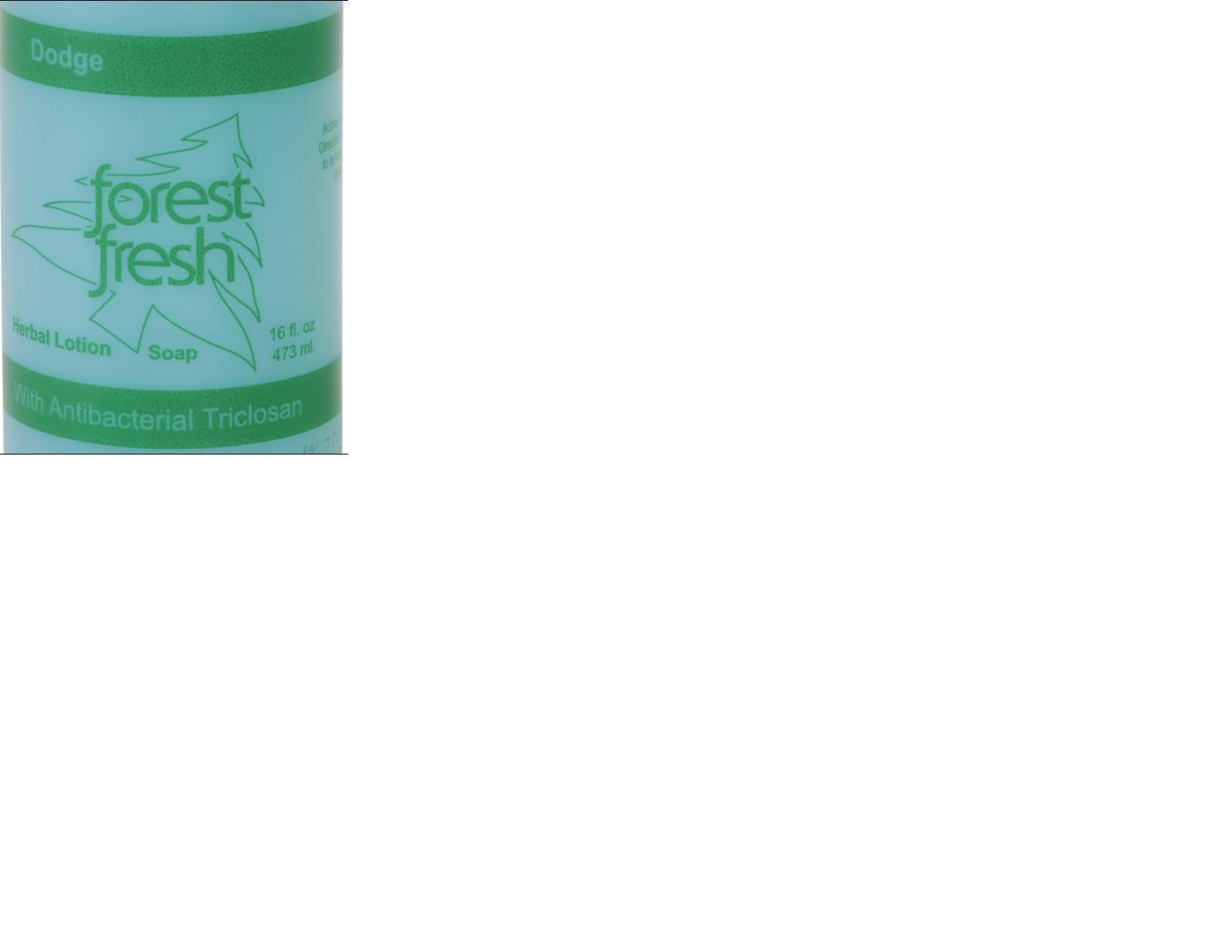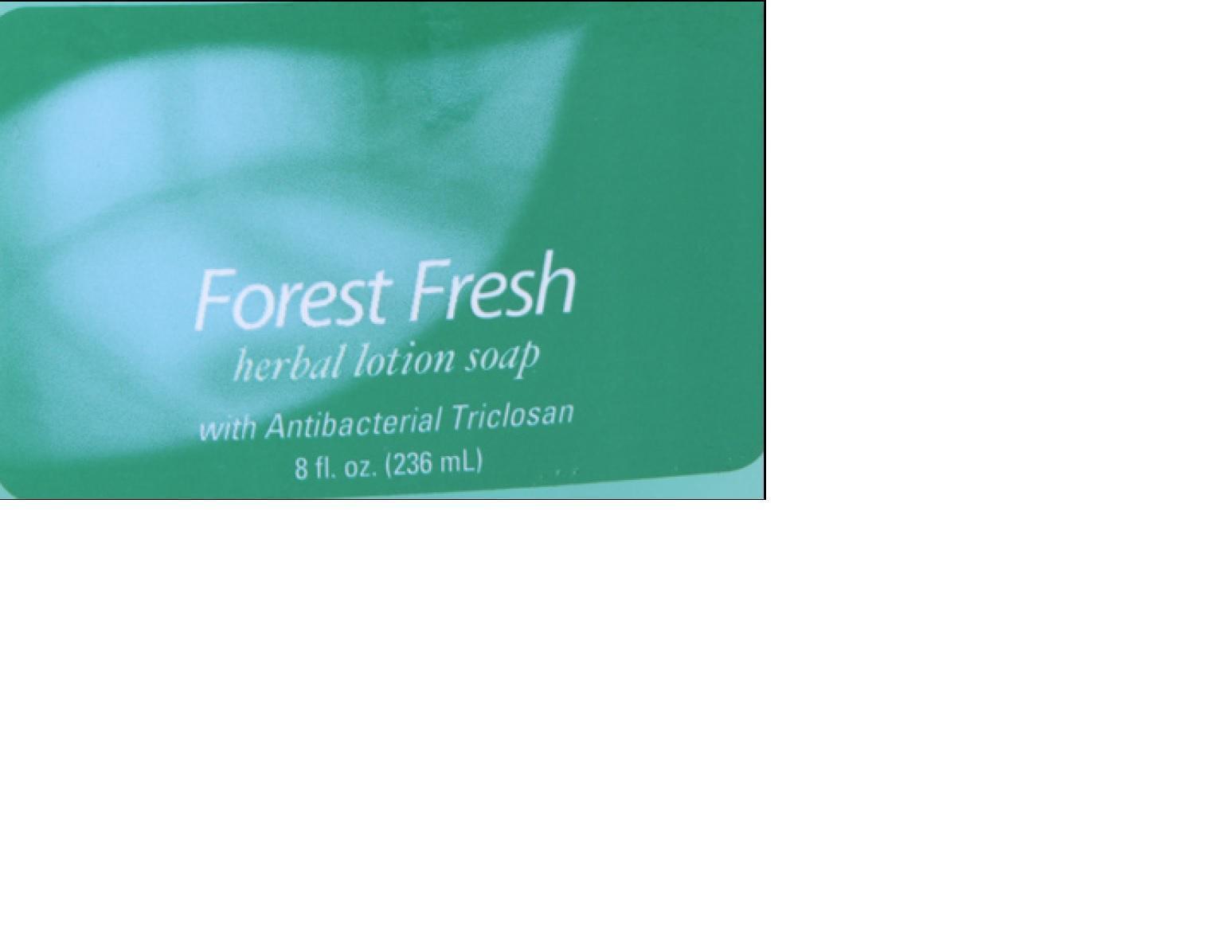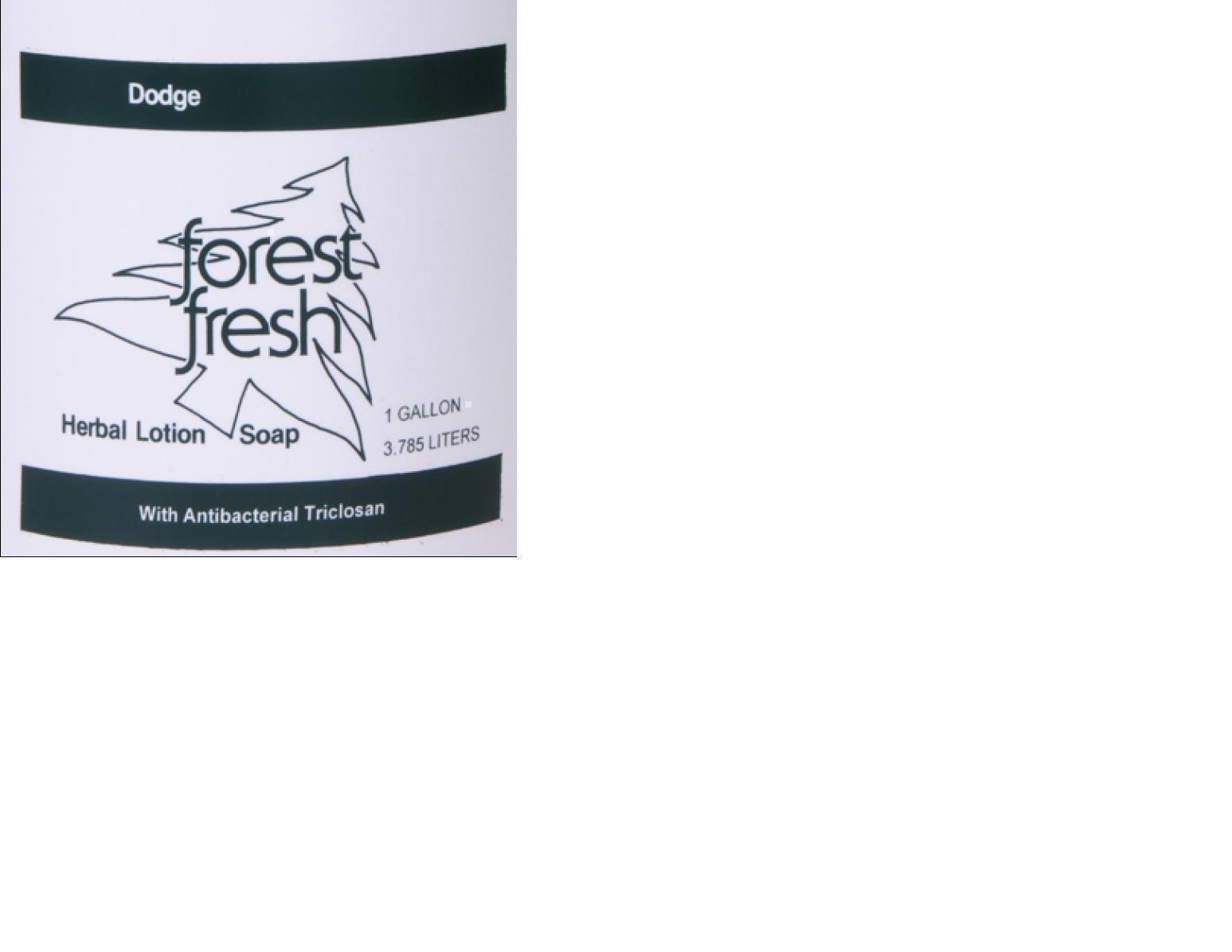 DRUG LABEL: Forest Fresh
NDC: 25113-222 | Form: SOAP
Manufacturer: The Dodge Company, Inc.
Category: otc | Type: HUMAN OTC DRUG LABEL
Date: 20140425

ACTIVE INGREDIENTS: TRICLOSAN 0.004 g/1 g
INACTIVE INGREDIENTS: COCO DIETHANOLAMIDE; FD&C BLUE NO. 1; potassium cocoate; MYRISTAMINE OXIDE; COCAMIDOPROPYL BETAINE; IMIDUREA; SODIUM LAURYL SULFATE; SODIUM C14-16 OLEFIN SULFONATE; SODIUM CHLORIDE; CITRIC ACID MONOHYDRATE; WATER; PROPYLENE GLYCOL

Forest Fresh

WARNINGS SECTION

1) For external use only.

2) Do not use in the eyes.

3) Discontinue use if irritation and redness develop. If condition persists for more than 72 hours consult a doctor.

OTC - KEEP OUT OF REACH OF CHILDREN SECTION

Keep out of reach of children. If swallowed, get medical help or contact a Poison Control Center right away.

INDICATIONS & USAGE SECTION

Antiseptic handwash for handwashing to decrease baceria on the skin.

OTC - PURPOSE SECTION

Antiseptic handwash

DOSAGE & ADMINISTRATION SECTION

Moisten surface to be cleaned, apply soap, rub to create lather, and rinse. Repeat as needed.

OTC - ACTIVE INGREDIENT SECTION

Triclosan

INACTIVE INGREDIENT SECTION

cocamidopropyl betaine

cocodiethanolamide

citric acid monohydrate

FD&C blue No.1

imidazolidinyl urea

myristamine oxide

potassium cocoate

propylene glycol

sodium C14-C16 olefin sulfonate

sodium chloride

sodium lauryl sulfate

water

PACKAGE LABEL.PRINCIPAL DISPLAY PANEL

Forest Fresh 8oz.jpg

PACKAGE LABEL.PRINCIPAL DISPLAY PANEL

Forest Fresh 16oz.jpg

PACKAGE LABEL.PRINCIPAL DISPLAY PANEL

Forest Fresh Gal.jpg